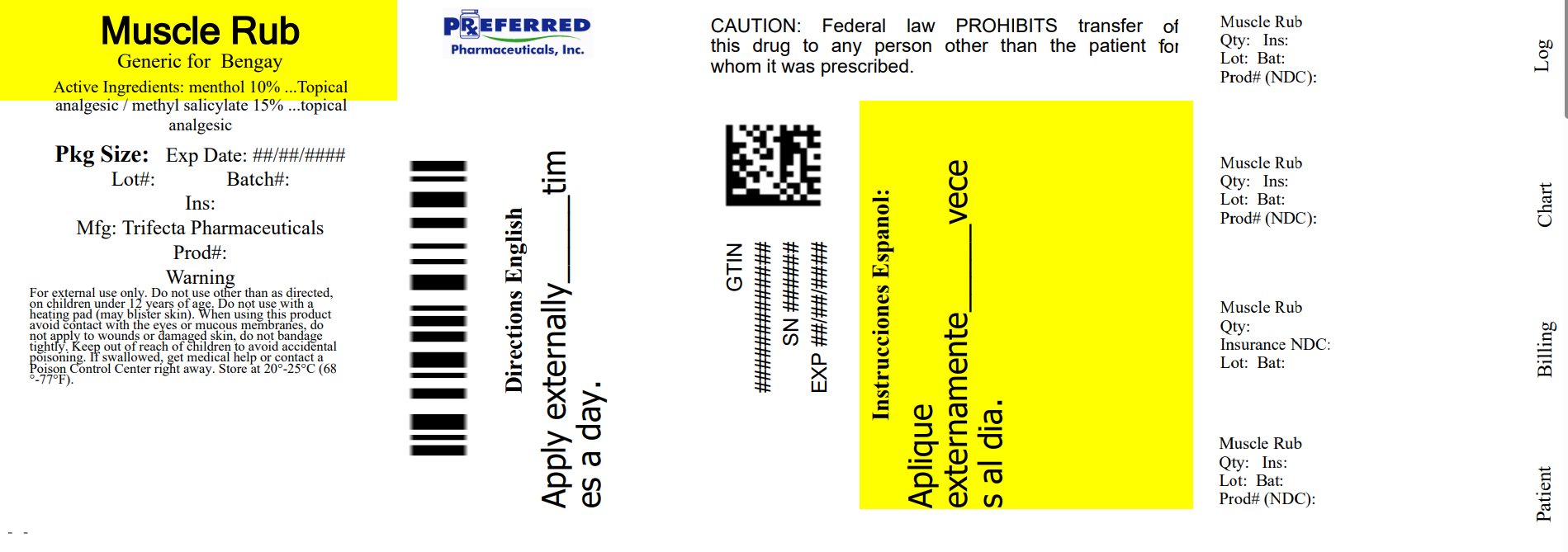 DRUG LABEL: Muscle Rub Cream
NDC: 68788-8544 | Form: CREAM
Manufacturer: Preferred Pharmaceuticals Inc.
Category: otc | Type: HUMAN OTC DRUG LABEL
Date: 20250818

ACTIVE INGREDIENTS: MENTHOL, UNSPECIFIED FORM 10 g/100 g; METHYL SALICYLATE 15 g/100 g
INACTIVE INGREDIENTS: POLYSORBATE 80; TROLAMINE; PROPYLPARABEN; CARBOMER HOMOPOLYMER TYPE C (ALLYL PENTAERYTHRITOL CROSSLINKED); CETYL ALCOHOL; GLYCERYL MONOSTEARATE; METHYLPARABEN; WATER; STEARIC ACID; GLYCERIN

Globe Muscle Rub Cream

Active Ingredient

Menthol 10%

Active Ingredient

Methyl Salicylate 15%

PURPOSE

Topical Analgesic

INDICATIONS AND USAGE

For the temporary relief of minor aches and pains of muscles and joints associated with simple backache, arthritis, strains, bruises and sprains

Warnings

For external use only

Do not use:

- On wounds or damaged, broken, (open) or irritated skin
- With a heating pad

Ask a doctor before use if you are pregnant or breast feeding.

When using this product

- Avoid contact with eyes or mucous membrane
- Do not bandage tightly

Stop Use and ask a doctor

- Conditions worsens or does not improve within 7 days
- Symptoms clear up and occur again within a few days
- Excessive skin irritation develops

A temporary burning sensation may occur upon application, but generally disappears in a few days

Keep out of the reach of Children

If swallowed, get medical help or contact a Poison Control Center immediately

Directions

- Adults and children 12 years of age or older. Apply to the affected area not more than 3 to 4 times daily.

Children under 12 years of age. consult a doctor

- Unless treating hands, wash hands thoroughly with soap and water immediately after use.

Other Information

- Store at controlled room temperature 20º-25ºC (68º-77ºF)

Questions ? Call 1-888-296-9067

Inactive Ingredients

Carbomer 940, Cetyl alcohol, Glycerol, Glyceryl monostearate, Methylparaben, Polysorbate 80, Propylparaben, Purified Water, Stearic acid, Trolamine

Distributed By

Trifecta Pharmaceuticals USA, LLC.

101 NE Third Avenue, Suite 1500

Ft. Lauderdale, FL. 33301

www.trifecta-pharma.com

Made in China

This product is not manufactured or distributed by Johnson & Johnson Consumer Products Company, a division of Johnson & Johnson consumer companies Inc. owner of the registered trademark BENGAY®.

Relabeled By: Preferred Pharmaceuticals Inc.
NDC 68788-8544-8